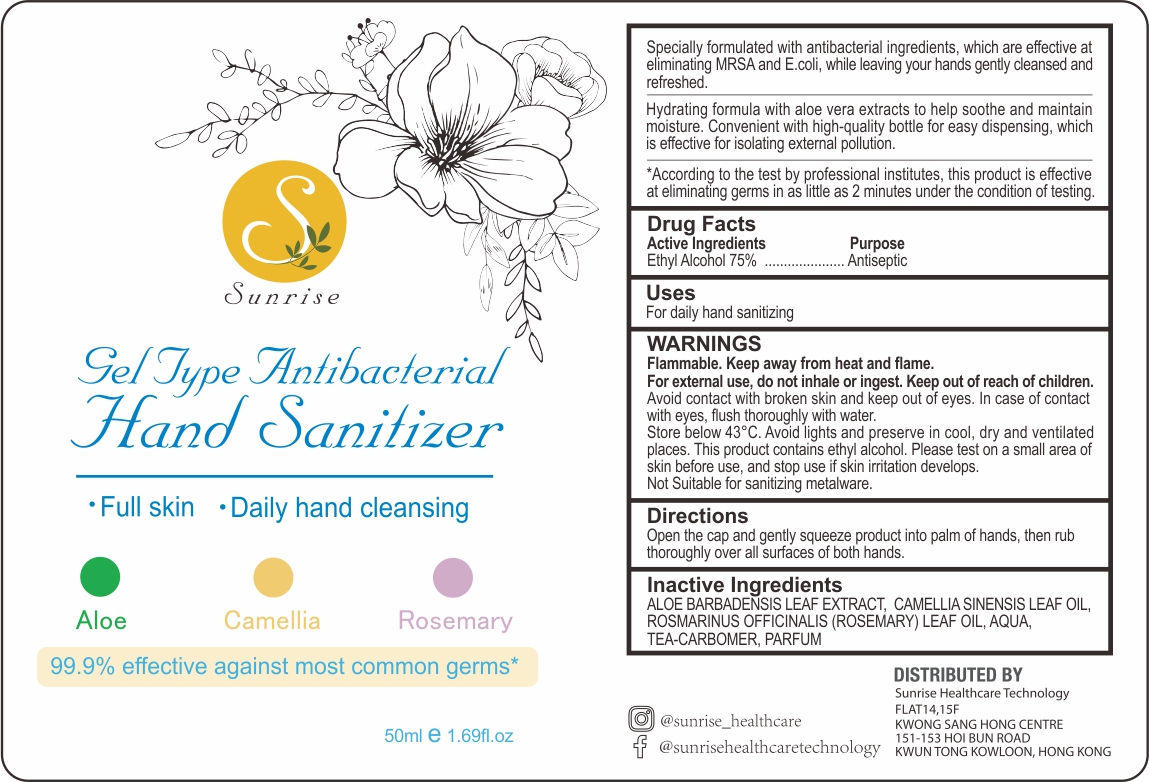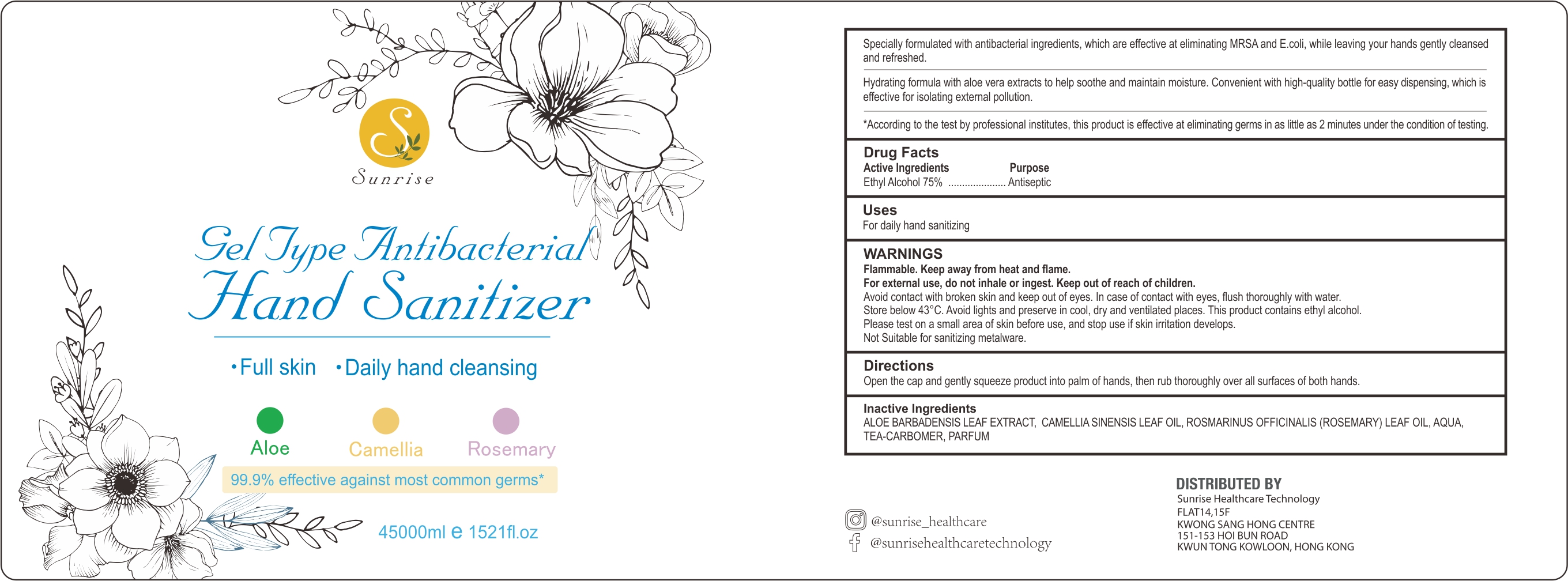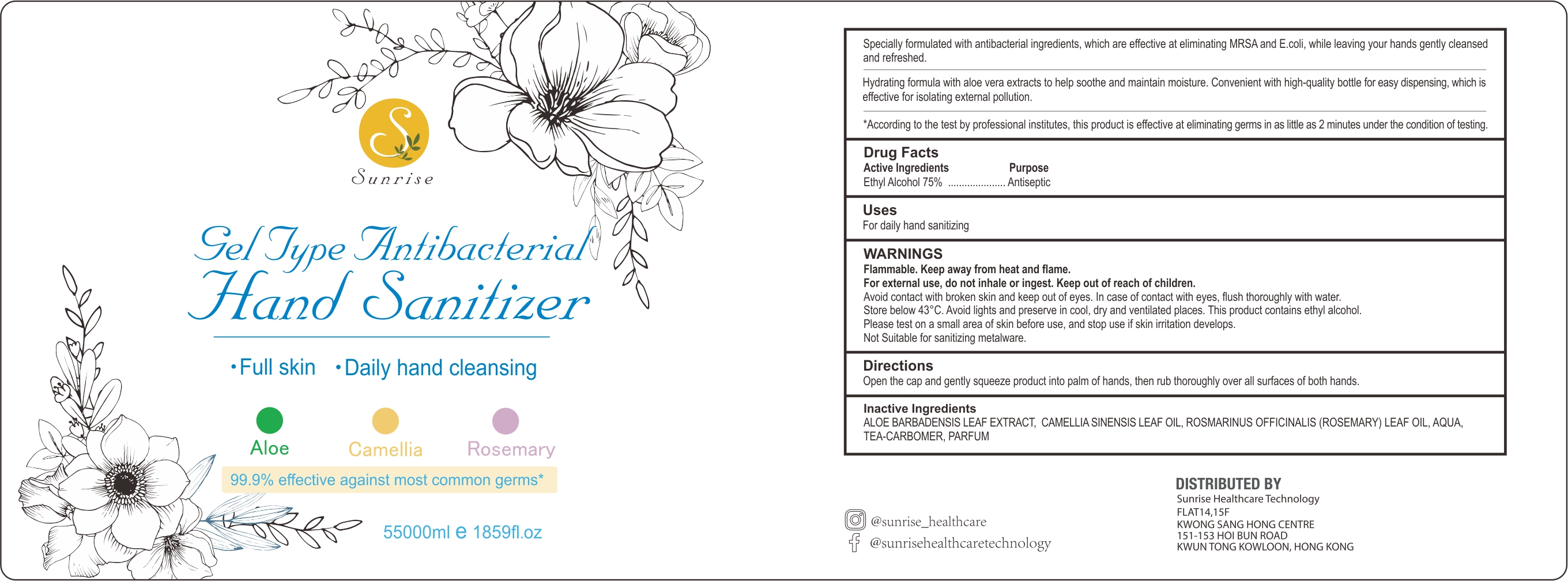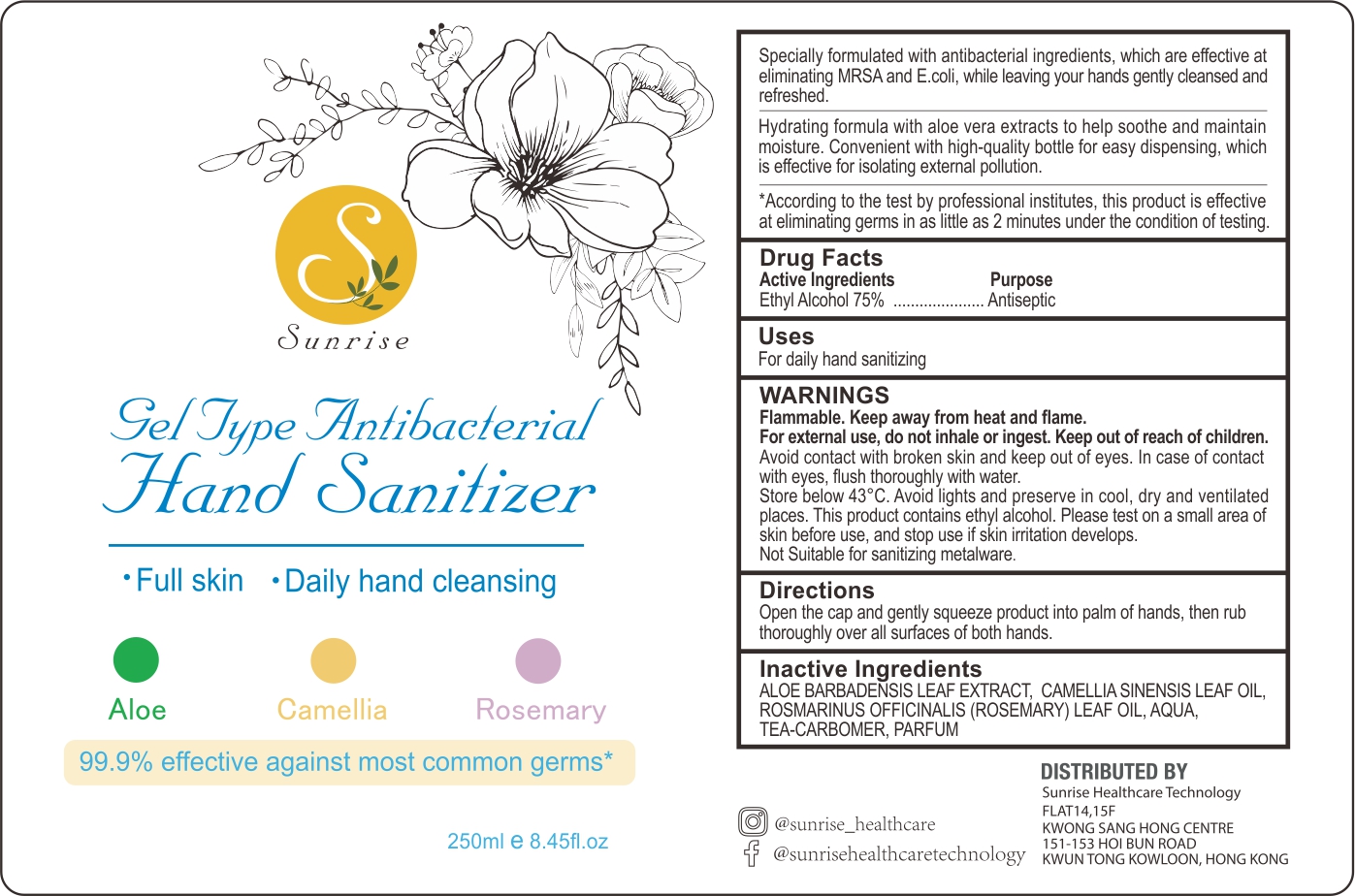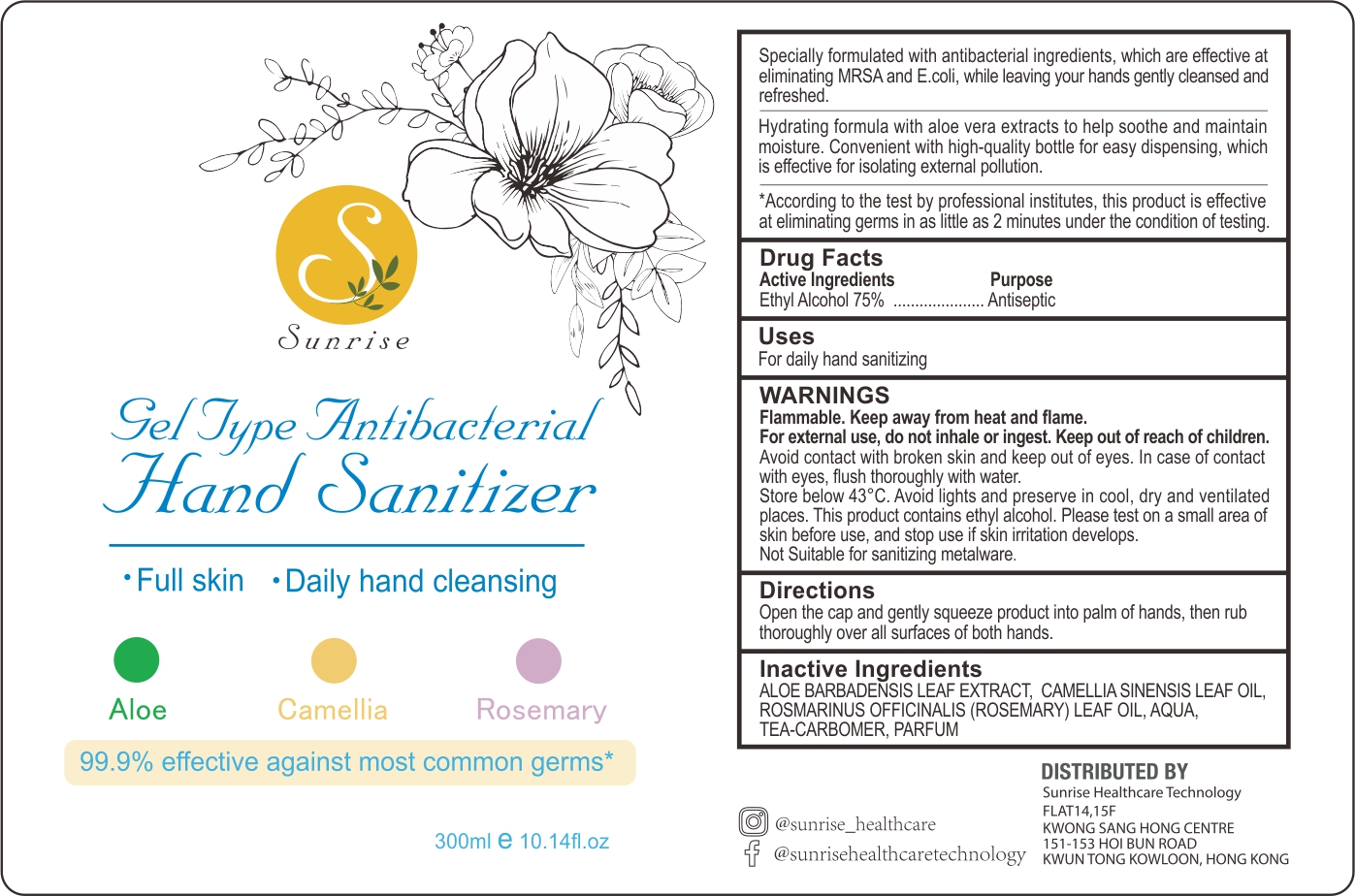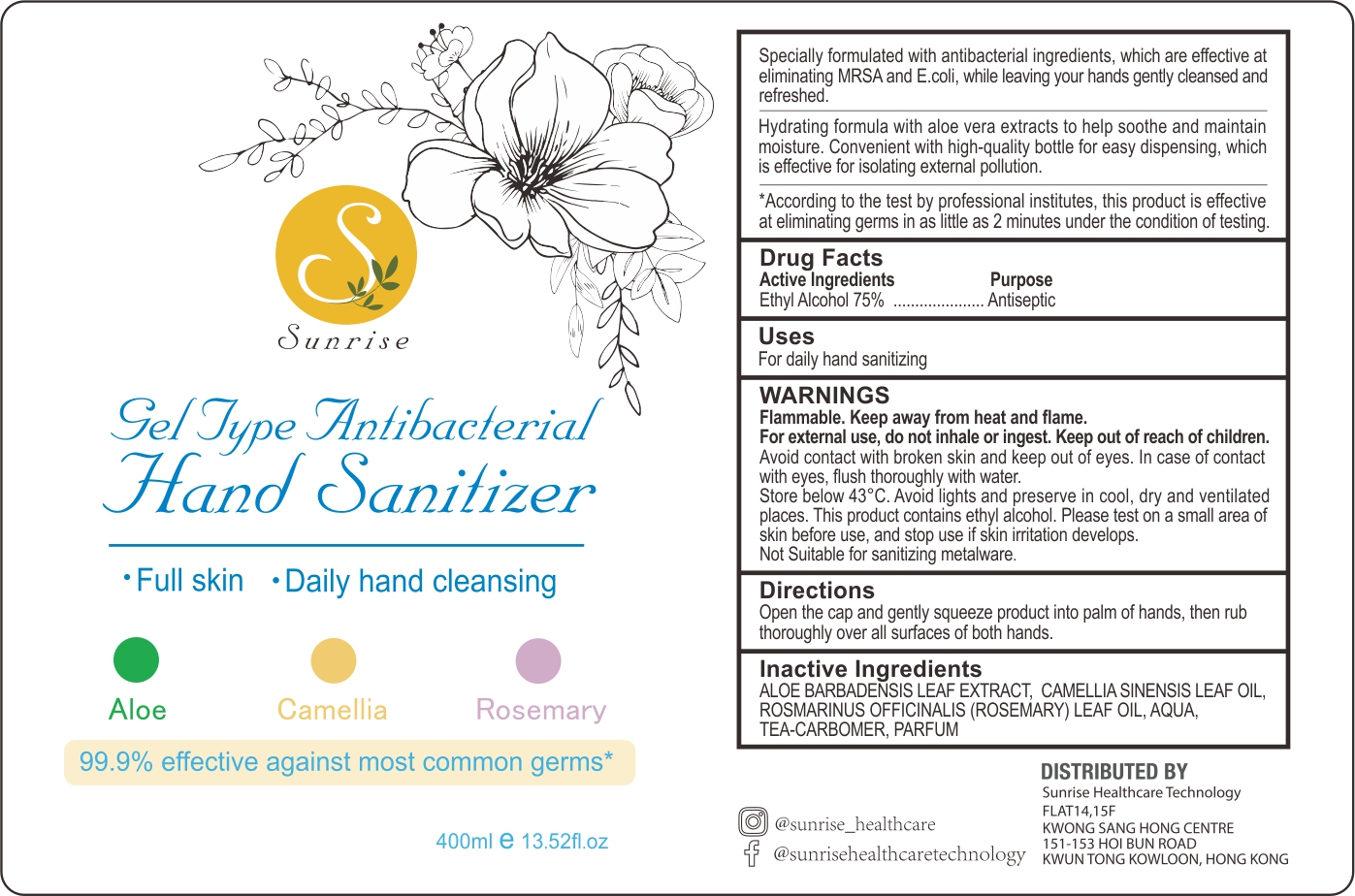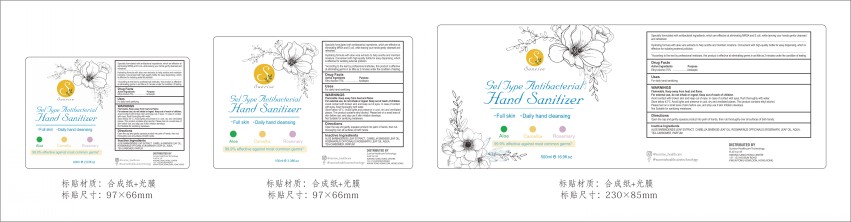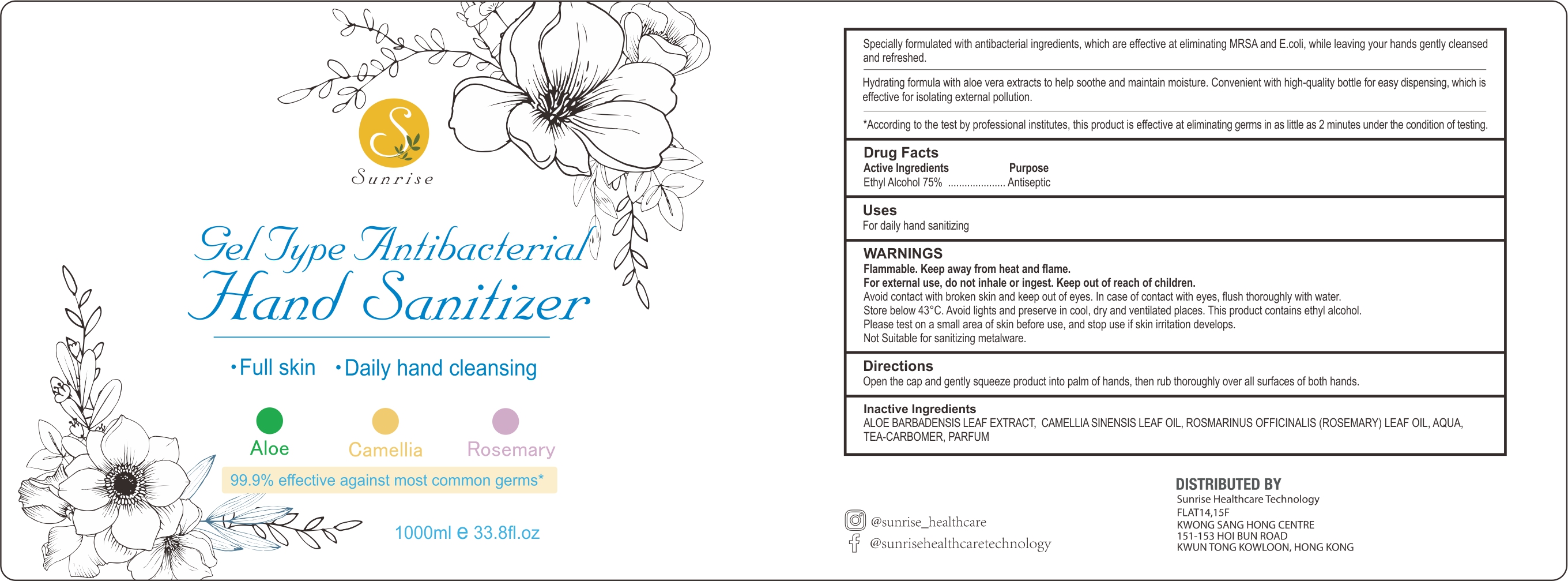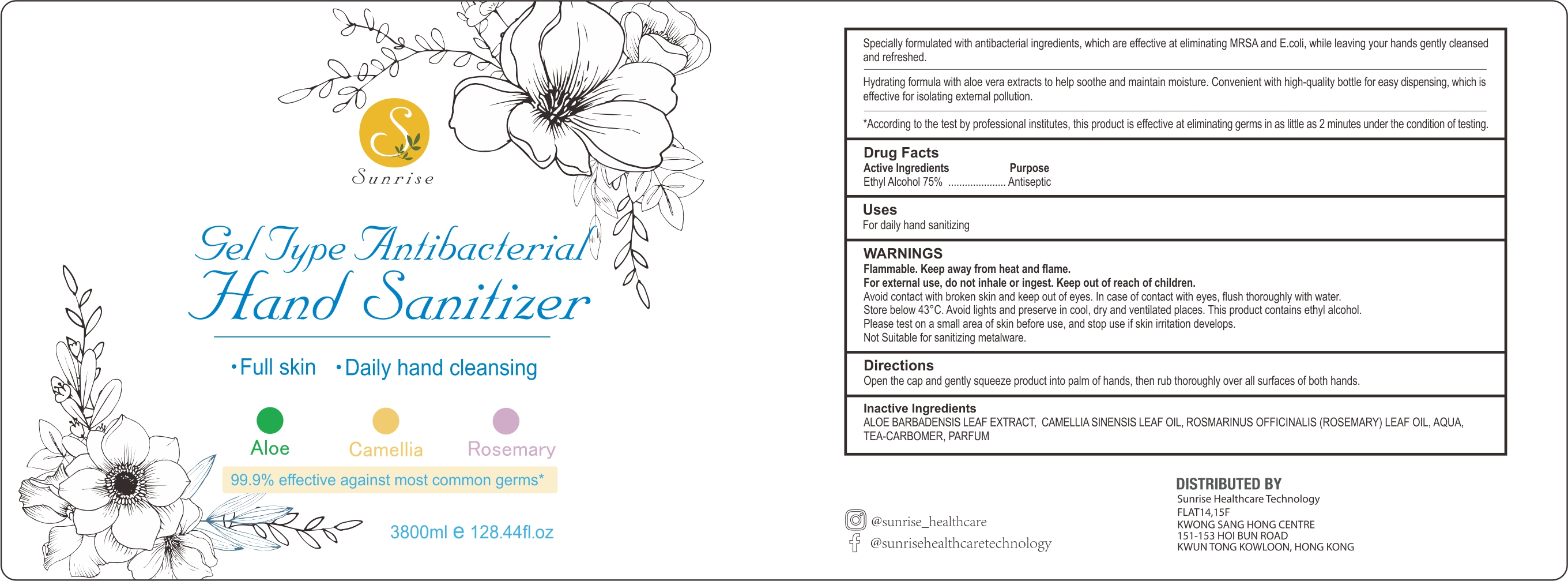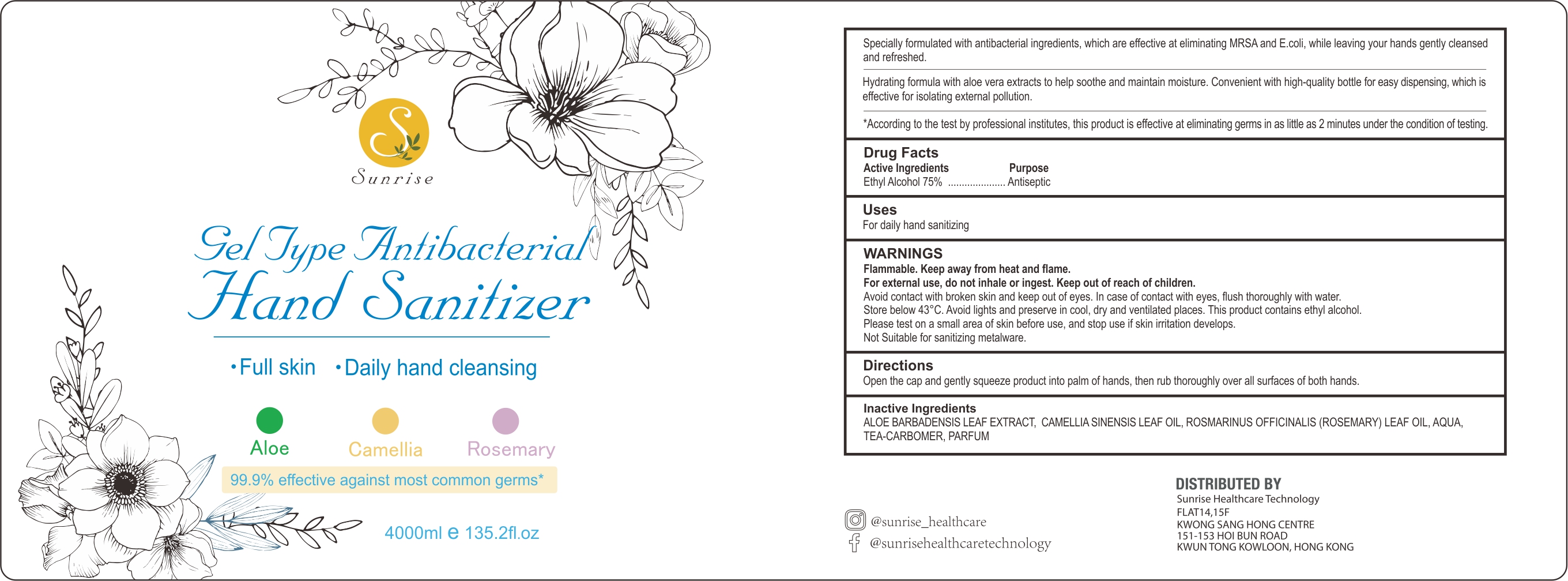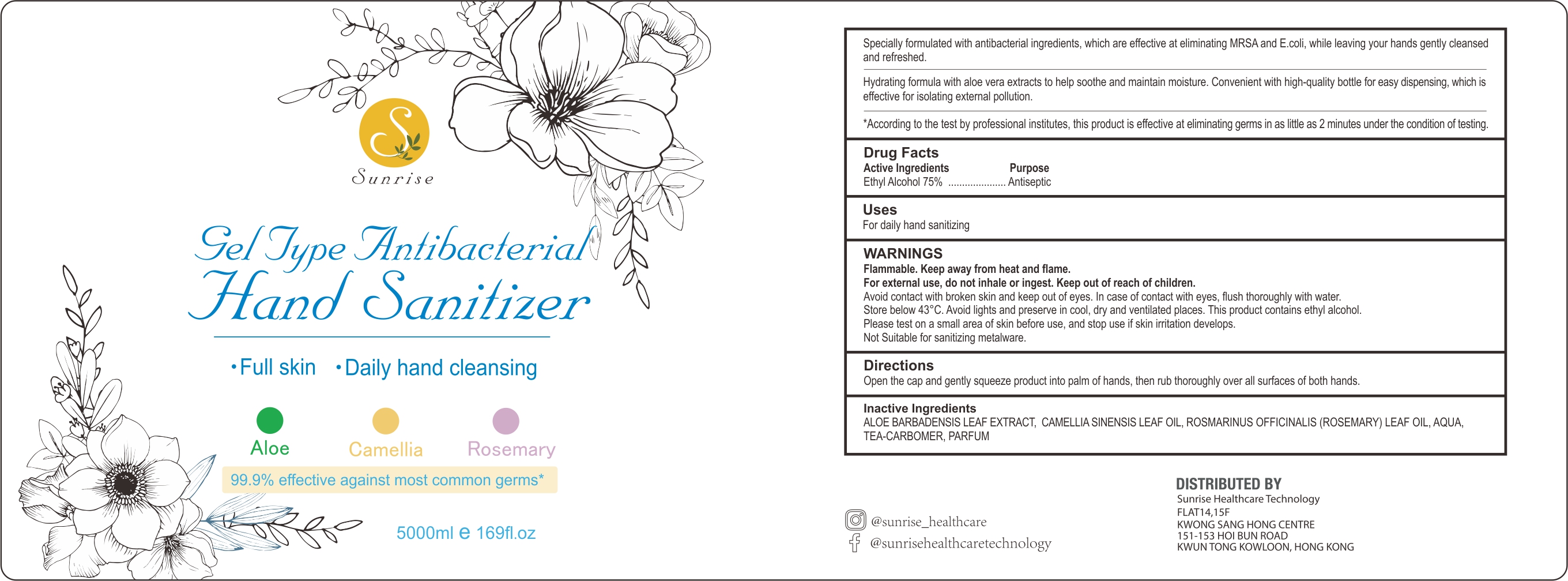 DRUG LABEL: Antibacterial Hand Sanitizer
NDC: 74743-008 | Form: GEL
Manufacturer: Guangzhou Joy Claire Biological Technology Co., Ltd
Category: otc | Type: HUMAN OTC DRUG LABEL
Date: 20200629

ACTIVE INGREDIENTS: ALCOHOL 75 mL/100 mL
INACTIVE INGREDIENTS: ROSEMARY OIL; ALOE VERA LEAF; TEA LEAF OIL; WATER

Antibacterial Hand Sanitizer

SUMMARY OF SAFETY AND EFFECTIVENESS

Specially formulated with antibacterial ingredients, which are effective at eliminating MRSA and E.coli while leaving your hands

gently cleansed and refreshed.

Hydrating formula with aloe vera extracts to help soothe and maintain moisture.Convenient with high-quality bottle for easy dispensing, which is effective for isolating external pollution.

According to the test by professional institutes, this product is effective at eliminating germs in as little as 2 minutes under the condition of testing.

Active Ingredients

Ethyl Alcohol 75%

Purpose

Antiseptic

Uses

For daily hand sanitizing

WARNINGS

Flammable.Keep away from heat and flame.

For external use, do not inhale or ingest.Keep out of reach of children.

Avoid contact wih broken skin and keep out of eyes.In case of contact with eyes, flush thoroughly with water.

Store below 43°C.Avoid lights and preserve in cool,dry and ventilated places.This product contains ethyl alcohol.

Please test on a small area of skin before use,and stop use if skin irritation develops.

Not Suitable for sanitizing metalware.

Directions

Open the cap and gently squeeze product into palm of hands, then rub thoroughly over all surfaces of both hands.

Inactive Ingredients

ALOE BARBADENSIS LEAF EXTRACT,CAMELLIA SINENSIS LEAF OIL,

ROSMARINUS OFFICINALIS(ROSEMARY) LEAF OIL,AQUA,

TEA-CARBOMER, PARFUM